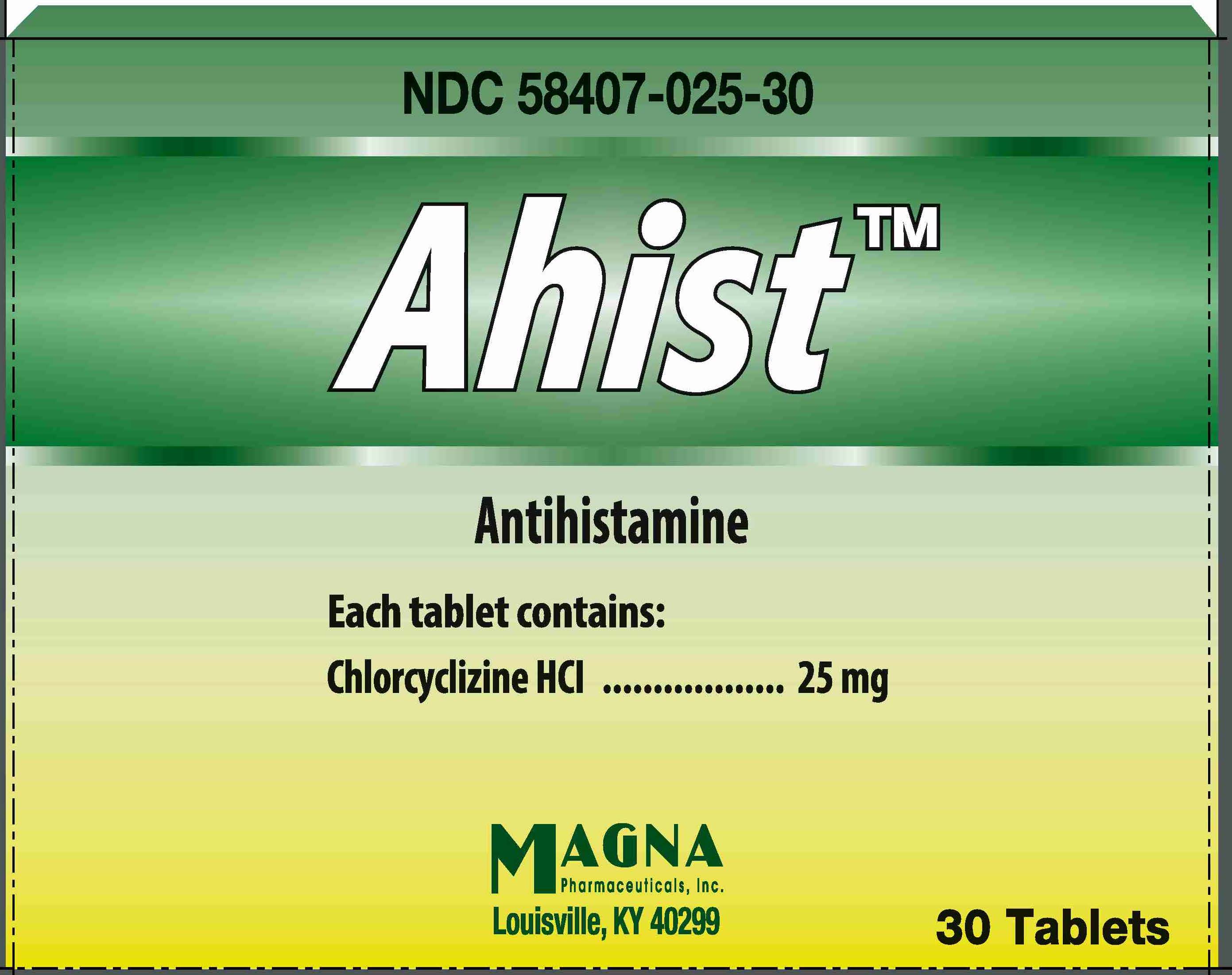 DRUG LABEL: AHIST
NDC: 58407-025 | Form: TABLET
Manufacturer: Magna Pharmaceutcals, Inc.
Category: otc | Type: HUMAN OTC DRUG LABEL
Date: 20220817

ACTIVE INGREDIENTS: CHLORCYCLIZINE HYDROCHLORIDE 25 mg/1 1
INACTIVE INGREDIENTS: MAGNESIUM STEARATE; CELLULOSE, MICROCRYSTALLINE; SODIUM STARCH GLYCOLATE TYPE A POTATO

AHIST™

Drug Facts

Active Ingredients (in each immediate-release tablet)

Chlorcyclizine HCl 25 mg

Purpose

Antihistamine

Uses

temporarily relieves these symptoms due to hay fever or other upper respiratory allergies:

- runny nose
- sneezing
- itching of the nose or throat
- itchy, watery eyes

Warnings

Do not exceed recommended dosage.

DO NOT USE

Do not take this product unless directed by a doctor if you have

- a breathing problem such as emphysema or chronic bronchitis
- glaucoma
- difficulty in urination due to enlargement of the prostate gland

Ask a doctor before use if you are taking sedatives or tranquilizers

When using this product

- excitability may occur, especially in children
- may cause drowsiness
- alcohol, sedatives and tranquilizers may increase drowsiness effect
- Use caution when driving a motor vehicle or operating machinery.

PREGNANCY OR BREAST FEEDING

If pregnant or breast-feeding, ask a health professional before use.

Keep out of reach of children.

In case of accidental overdose, seek professional help or contact a Poison Control Center immediately.

Directions

Do not exceed recommended dosage.

Adults and children 12 years of age and over: | 1 tablet by mouth every 6-8 hours, not to exceed 3 tablets in 24 hours, or as directed by a doctor
Children 6 to under 12 years of age: | ½ tablet by mouth every 6-8 hours, not to exceed 1½ tablets in 24 hours, or as directed by a doctor
Children under 6 years of age | Consult a doctor

Inactive ingredients

Lake Blend Green, Magnesium Stearate, Microcrystalline Cellulose, Sodium Starch Glycolate

Questions or Comments?

Call 1-888-206-5525

www.magnaweb.com

Rev. 12/12

Manufactured for:
MAGNA Pharmaceuticals, Inc.
Louisville, KY 40299

PRINCIPAL DISPLAY PANEL - 30 Tablet Carton

NDC 58407-025-30

AHIST™

Antihistamine

Each tablet contains:

Chlorcyclizine HCl 25 mg

MAGNA Pharmaceuticals, Inc.
Louisville, KY 40299

30 Tablets